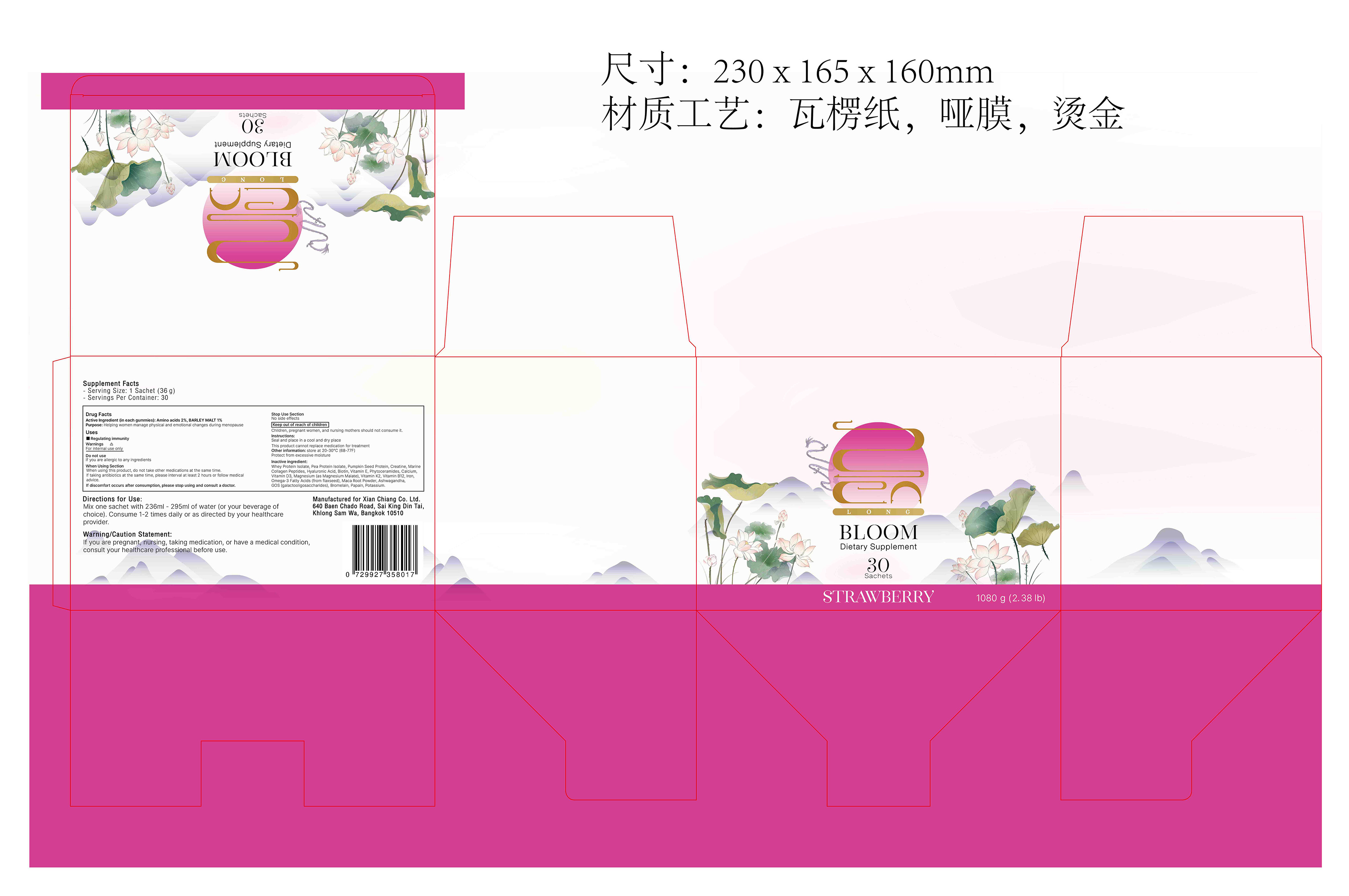 DRUG LABEL: Bloom powder Strawberry flavor
NDC: 83739-008 | Form: POWDER
Manufacturer: XIAN CHIANG COMPANY LIMITED
Category: otc | Type: HUMAN OTC DRUG LABEL
Date: 20250701

ACTIVE INGREDIENTS: BARLEY MALT 1 g/100 g; AMINO ACIDS 2 g/100 g
INACTIVE INGREDIENTS: POTASSIUM; CREATINE; MARINE COLLAGEN, SOLUBLE; HYALURONIC ACID; BIOTIN; .ALPHA.-TOCOPHEROL; SOY SPHINGOLIPIDS; CALCIUM; CHOLECALCIFEROL; MAGNESIUM MALATE; MENAQUINONE 6; CYANOCOBALAMIN; LEPIDIUM MEYENII ROOT; 4'-GALACTOSYLLACTOSE; PAPAIN; PUMPKIN SEED; WITHANIA SOMNIFERA ROOT; OMEGA-3 FATTY ACIDS; WHEY; STRAWBERRY JUICE; PEA PROTEIN; BROMELAIN; IRON

008

ACTIVE INGREDIENT

Amino acids 2%, BARLEY MALT 1%

PURPOSE

Purpose: Helping women manage physical and emotional changes during menopause

INDICATIONS AND USAGE

Regulating immunity

Warnings:

For internal use only

Warning/Caution Statement:If you are pregnant, nursing, taking medication, or have a medical condition, consult your healthcare professional before use.

DO NOT USE

If you are allergic to any ingredients

When using this product, do not take other medications at the same time.If taking antibiotics at the same time, please interval at least 2 hours or follow medical advice.

If discomfort occurs after consumption, please stop using and consult a doctor.

STOP USE

No side effects.

Keep out of reach of children

Children, pregnant women, and nursing mothers should not consume it.

DOSAGE AND ADMINISTRATION

Directions for Use:Mix one sachet with 236ml - 295ml of water (or your beverage of choice). Consume 1-2 times daily or as directed by your healthcare provider.

STORAGE AND HANDLING

Instructions:Seal and place in a cool and dry placeThis product cannot replace medication for treatment

Other information: store at 20-30°℃ (68-77F) Protect from excessive moisture

INACTIVE INGREDIENT

Whey Protein Isolate, Pea Protein Isolate, Pumpkin Seed Protein, Creatine, Marine Collagen Peptides, Hyaluronic Acid, Biotin, Vitamin E, Phytoceramides, Calcium, Vitamin D3, Magnesium (as Magnesium Malate), Vitamin K2, Vitamin B12, Iron, Omega-3 Fatty Acids (from flaxseed), Maca Root Powder, Ashwagandha, GOS (galactooligosaccharides), Bromelain, Papain, Potassium.